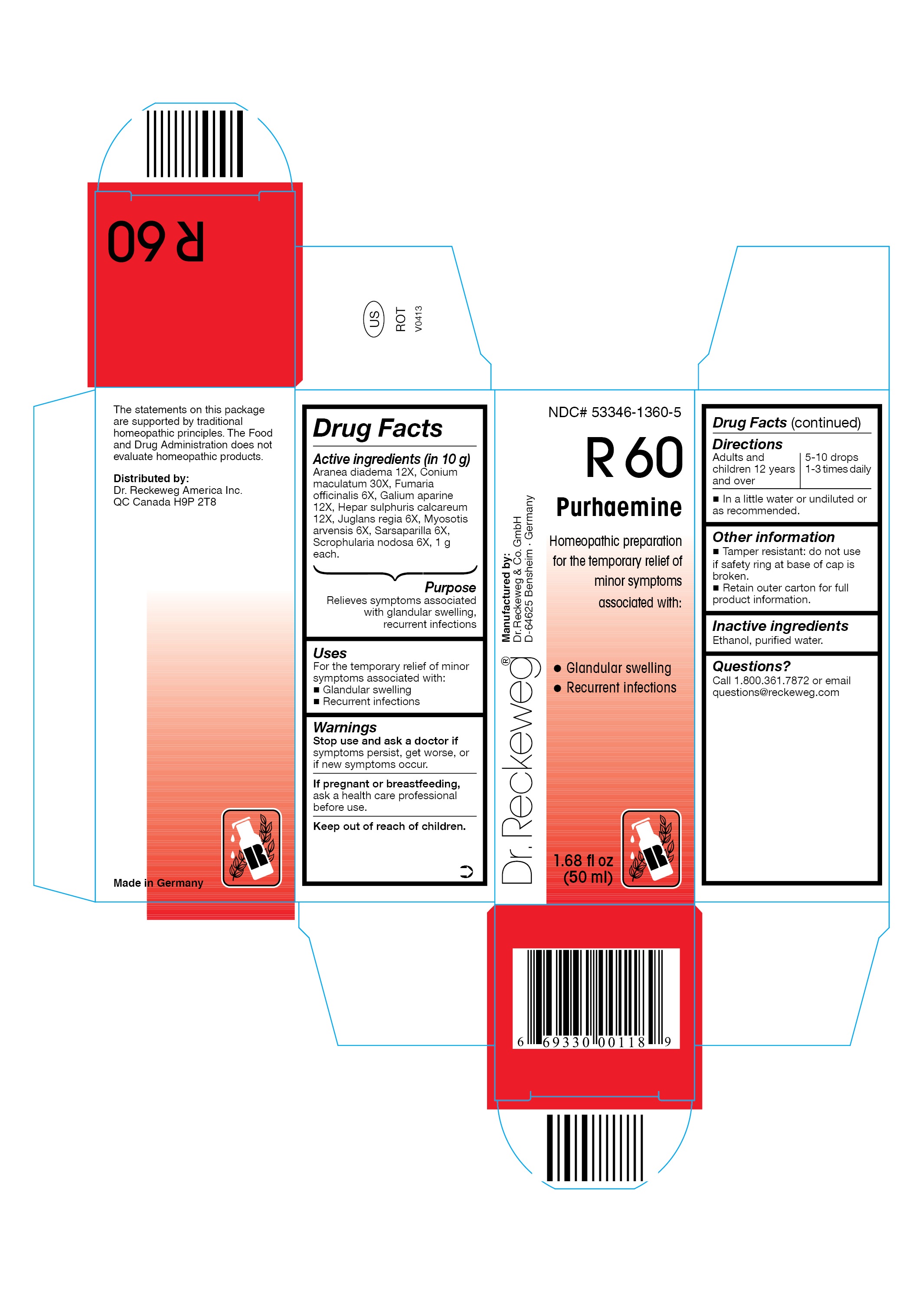 DRUG LABEL: DR. RECKEWEG R60 Purhaemine
NDC: 53346-1360 | Form: LIQUID
Manufacturer: PHARMAZEUTISCHE FABRIK DR. RECKEWEG & CO
Category: homeopathic | Type: HUMAN OTC DRUG LABEL
Date: 20130404

ACTIVE INGREDIENTS: ARANEUS DIADEMATUS 12 [hp_X]/50 mL; CONIUM MACULATUM FLOWERING TOP 30 [hp_X]/50 mL; FUMARIA OFFICINALIS FLOWERING TOP 6 [hp_X]/50 mL; GALIUM APARINE 12 [hp_X]/50 mL; CALCIUM SULFIDE 12 [hp_X]/50 mL; ENGLISH WALNUT 6 [hp_X]/50 mL; MYOSOTIS ARVENSIS 6 [hp_X]/50 mL; SMILAX REGELII ROOT 6 [hp_X]/50 mL; SCROPHULARIA NODOSA 6 [hp_X]/50 mL
INACTIVE INGREDIENTS: ALCOHOL; WATER

DR. RECKEWEG R60 Purhaemine

Active ingredients

Aranea diadema 12X, Conium maculatum 30X, Fumaria officinalis 6X, Galium aparine 12X, Hepar sulphuris calcareum 12X Juglans regia 6X, Myosotis arvensis 6X, Sarsaparilla 6X, Scrophularia nodosa 6X, 1 g each in 10 g.

Purpose

Relieves symptoms associated with glandular swelling, recurrent infections

Uses

For the temporary relief of minor symptoms associated with:

- Glandular swelling
- Recurrent infections

Warnings

Stop use and ask a doctor if symptoms persist, get worse, or if new symptoms occur.

PREGNANCY OR BREAST FEEDING

If pregnant or breastfeeding, ask a health care professional before use.

Keep out of reach of children.

Directions
Adults and children ≥ 12 years 5-10 drops 1-3 times daily in a little water or undiluted or as recommended.

Other information

- Tamper resistant: do not use if safety ring at base of cap is broken.
- Retain outer carton for full product information.

Inactive ingredients

Ethanol, purified water.

Questions?

Call 1-800-361-7872 or email questions@reckeweg.com

PACKAGE LABEL

NDC# 53346-1360-5

Dr. Reckeweg R60 Purhaemine

Homeopathic preparation for the temporary relief of minor symptoms associated with:

- Glandular swelling
- Recurrent infections

Manufactured by:

Dr. Reckeweg Co. GmbH

D-64625 Bensheim

Germany

1.68 fl oz
(50 ml)